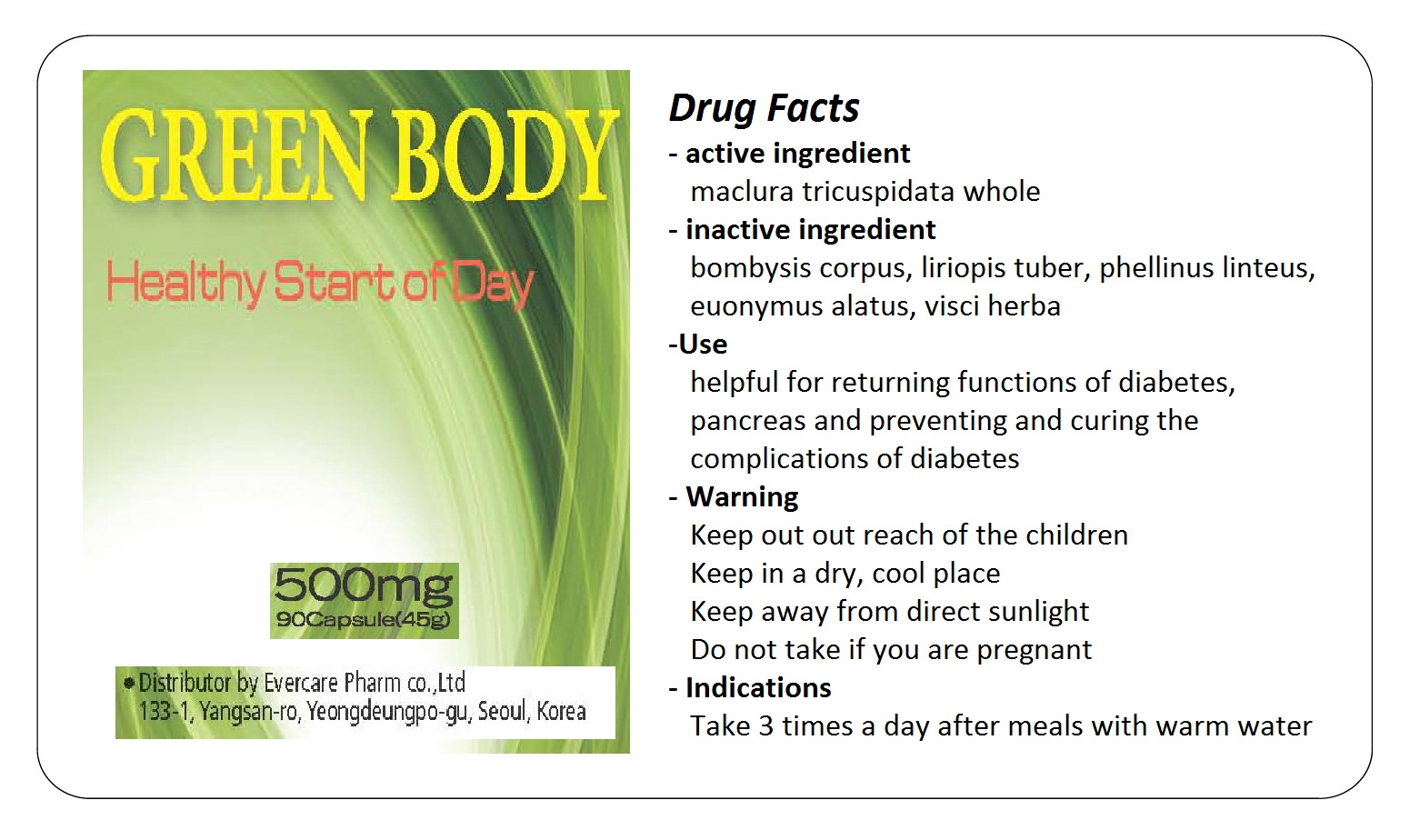 DRUG LABEL: Green Body
NDC: 42469-3001 | Form: TABLET
Manufacturer: Evercarepharm Co., Ltd
Category: otc | Type: HUMAN OTC DRUG LABEL
Date: 20120703

ACTIVE INGREDIENTS: MACLURA TRICUSPIDATA WHOLE 180 mg/1 1
INACTIVE INGREDIENTS: AMINO ACIDS, SILK; OPHIOPOGON JAPONICUS ROOT; PHELLINUS LINTEUS MYCELIUM; EUONYMUS ALATUS WHOLE; VISCUM ALBUM WHOLE

Drug Facts

active ingredient: maclura tricuspidata whole

inactive ingredient: bombysis corpus, liriopis tuber, phellinus linteus, euonymus alatus, visci herba

PURPOSE

helpful for returning functions of diabetes, pancreas and preventing and curing the complications of diabetes

keep out of reach of the children

INDICATIONS AND USAGE

take 3 times a day after meals with warm water

WARNINGS

keep in a dry, cool place
keep away from direct sunlight

DOSAGE AND ADMINISTRATION

do not take if you are pregnant